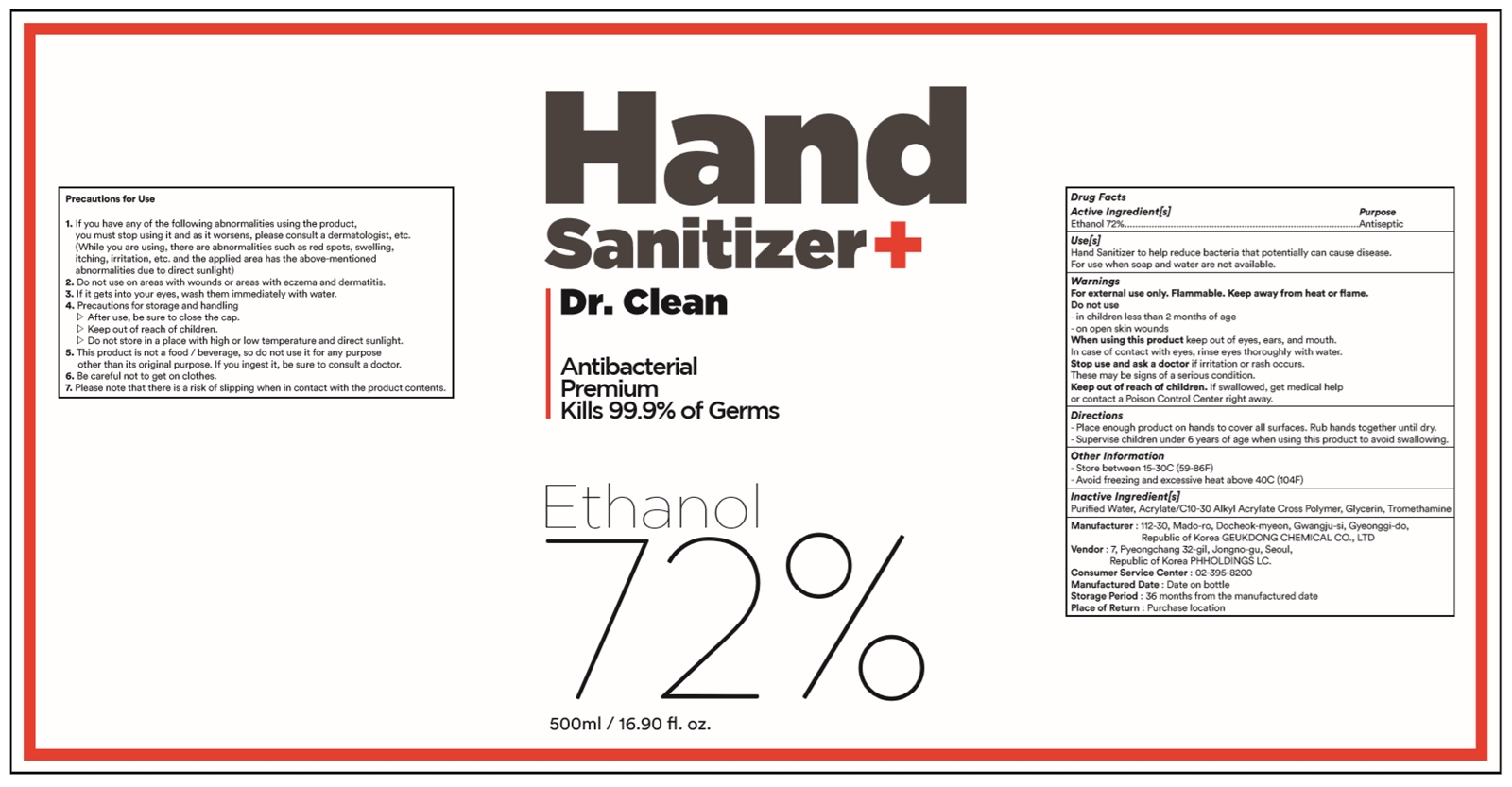 DRUG LABEL: Dr.Clean
NDC: 76850-201 | Form: GEL
Manufacturer: PH Holdings
Category: otc | Type: HUMAN OTC DRUG LABEL
Date: 20200425

ACTIVE INGREDIENTS: ALCOHOL 72 mL/100 mL
INACTIVE INGREDIENTS: GLYCERIN; CARBOMER INTERPOLYMER TYPE A (55000 CPS); TROMETHAMINE; WATER

Active Ingredient[s]

Ethanol 72%

Purpose

Antiseptic

Use[s]

Hand Sanitizer to help reduce bacteria that potentially can cause disease.

For use when soap and water are not available.

Warnings

For external use only. Flammable. Keep away from heat or flame.

Do not use

- in children less than 2 months of age

- on open skin wounds

When using this product

keep out of eyes, ears, and mouth.

Stop use and ask a doctor

if irritation or rash occurs. These may be signs of a serious condition.

Keep out of reach of children.

If swallowed, get medical help or contact a Poison Control Center right away.

Directions

- Place enough product on hands to cover all surfaces. Rub hands together until dry.

- Supervise children under 6 years of age when using this product to avoid swallowing.

Other Information

- Store between 15-30C (59-86F)

- Avoid freezing and excessive heat above 40C (104F)

Inactive Ingredient[s]

Purified Water, Acrylate/C10-30 Alkyl Acrylate Cross Polymer, Glycerin, Tromethamine

Precautions for Use

1. If you have any of the following abnormalities using the product,

you must stop using it and as it worsens, please consult a dermatologist, etc.

(While you are using, there are abnormalities such as red spots, swelling,

itching, irritation, etc. and the applied area has the above-mentioned

abnormalities due to direct sunlight)

2. Do not use on areas with wounds or areas with eczema and dermatitis.

3. If it gets into your eyes, wash them immediately with water.

4. Precautions for storage and handling

▷ After use, be sure to close the cap.

▷ Keep out of reach of children.

▷ Do not store in a place with high or low temperature and direct sunlight.

5. This product is not a food / beverage, so do not use it for any purpose

other than its original purpose. If you ingest it, be sure to consult a doctor.

6. Be careful not to get on clothes.

7. Please note that there is a risk of slipping when in contact with the product contents.